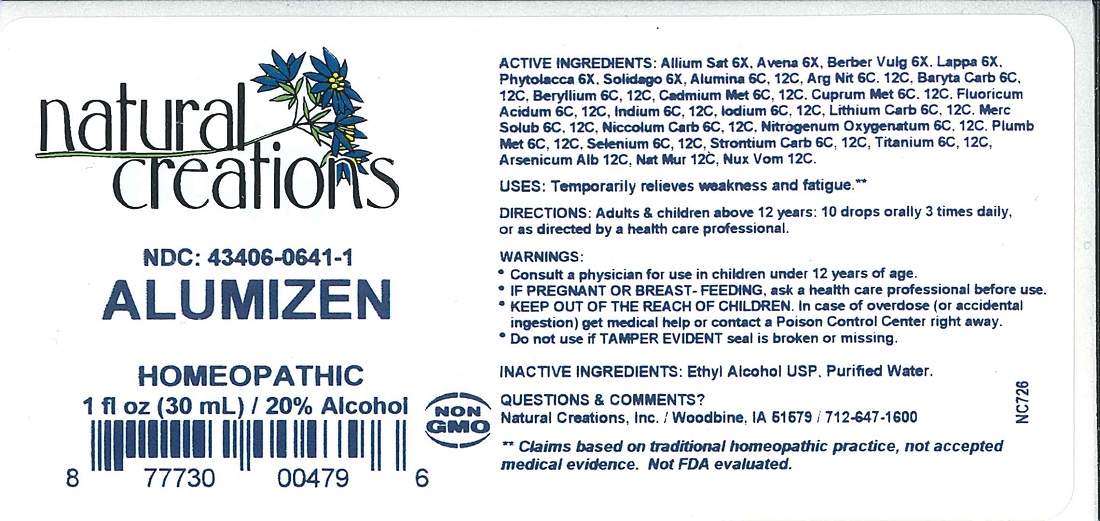 DRUG LABEL: ALUMIZEN
NDC: 43406-0641 | Form: LIQUID
Manufacturer: Natural Creations, Inc.
Category: homeopathic | Type: HUMAN OTC DRUG LABEL
Date: 20251113

ACTIVE INGREDIENTS: GARLIC 6 [hp_X]/1 mL; AVENA SATIVA FLOWERING TOP 6 [hp_X]/1 mL; BERBERIS VULGARIS ROOT BARK 6 [hp_X]/1 mL; ARCTIUM LAPPA ROOT 6 [hp_X]/1 mL; PHYTOLACCA AMERICANA ROOT 6 [hp_X]/1 mL; SOLIDAGO VIRGAUREA FLOWERING TOP 6 [hp_X]/1 mL; ALUMINUM OXIDE 12 [hp_C]/1 mL; SILVER NITRATE 12 [hp_C]/1 mL; BARIUM CARBONATE 12 [hp_C]/1 mL; BERYLLIUM 12 [hp_C]/1 mL; CADMIUM 12 [hp_C]/1 mL; copper 12 [hp_C]/1 mL; HYDROFLUORIC ACID 12 [hp_C]/1 mL; INDIUM 12 [hp_C]/1 mL; IODINE 12 [hp_C]/1 mL; LITHIUM CARBONATE 12 [hp_C]/1 mL; MERCURIUS SOLUBILIS 12 [hp_C]/1 mL; NICKEL CARBONATE HYDROXIDE TETRAHYDRATE 12 [hp_C]/1 mL; NITROUS OXIDE 12 [hp_C]/1 mL; lead 12 [hp_C]/1 mL; SELENIUM 12 [hp_C]/1 mL; STRONTIUM CARBONATE 12 [hp_C]/1 mL; TITANIUM 12 [hp_C]/1 mL; ARSENIC TRIOXIDE 12 [hp_C]/1 mL; SODIUM CHLORIDE 12 [hp_C]/1 mL; STRYCHNOS NUX-VOMICA SEED 12 [hp_C]/1 mL
INACTIVE INGREDIENTS: WATER; ALCOHOL

ALUMIZEN

ACTIVE INGREDIENT

ACTIVE INGREDIENTS: Allium Sat 6X, Avena 6X, Berber Vulg 6X, Lappa 6X, Phytolacca 6X, Solidago 6X, Alumina 6C, 12C, Arg Nit 6C, 12C, Baryta Carb 6C, 12C, Beryllium 6C, 12C, Cadmium Met 6C, 12C, Cuprum Met 6C, 12C, Fluoricum Acidum 6C, 12C, Indium 6C, 12C, Iodium 6C, 12C, Lithium Carb 6C, 12C, Merc Solub 6C, 12C, Niccolum Carb 6C, 12C, Nitrogenum Oxygenatum 6C, 12C, Plumb Met 6C, 12C, Selenium 6C, 12C, Strontium Carb 6C, 12C, Titanium 6C, 12C, Arsenicum Alb 12C, Nat Mur 12C, Nux Vom 12C.

PURPOSE

USES: Temporarily relieves weakness and fatigue.**

INDICATIONS AND USAGE

USES: Temporarily relieves weakness and fatigue.**

DOSAGE AND ADMINISTRATION

DIRECTIONS: Adults & children above 12 years: 10 drops orally 3 times daily, or as directed by a health care professional.

KEEP OUT OF REACH OF CHILDREN

KEEP OUT OF THE REACH OF CHILDREN. In case of overdose (or accidental ingestion) get medical help or contact a Poison Control Center right away.

WARNINGS:

* Consult a physician for use in children under 12 years of age.

* IF PREGNANT OR BREAST-FEEDING, ask a health care professional before use.

* KEEP OUT OF THE REACH OF CHILDREN. In case of overdose (or accidental ingestion) get medical help or contact a Poison Control Center right away.

* Do not use if TAMPER EVIDENT seal is broken or missing.

INACTIVE INGREDIENTS: Ethyl Alcohol USP, Purified Water.

QUESTIONS & COMMENTS?

Natural Creations, Inc. / Woodbine, IA 51579 / 712-647-1600

REFERENCES

** Claims based on traditional homeopathic practice, not accepted medical evidence. Not FDA evaluated.

PACKAGE LABEL

NDC: 43406-0641-1

ALUMIZEN

HOMEOPATHIC

1 fl oz (30 mL) / 20% Alcohol

UPC: 877730004796